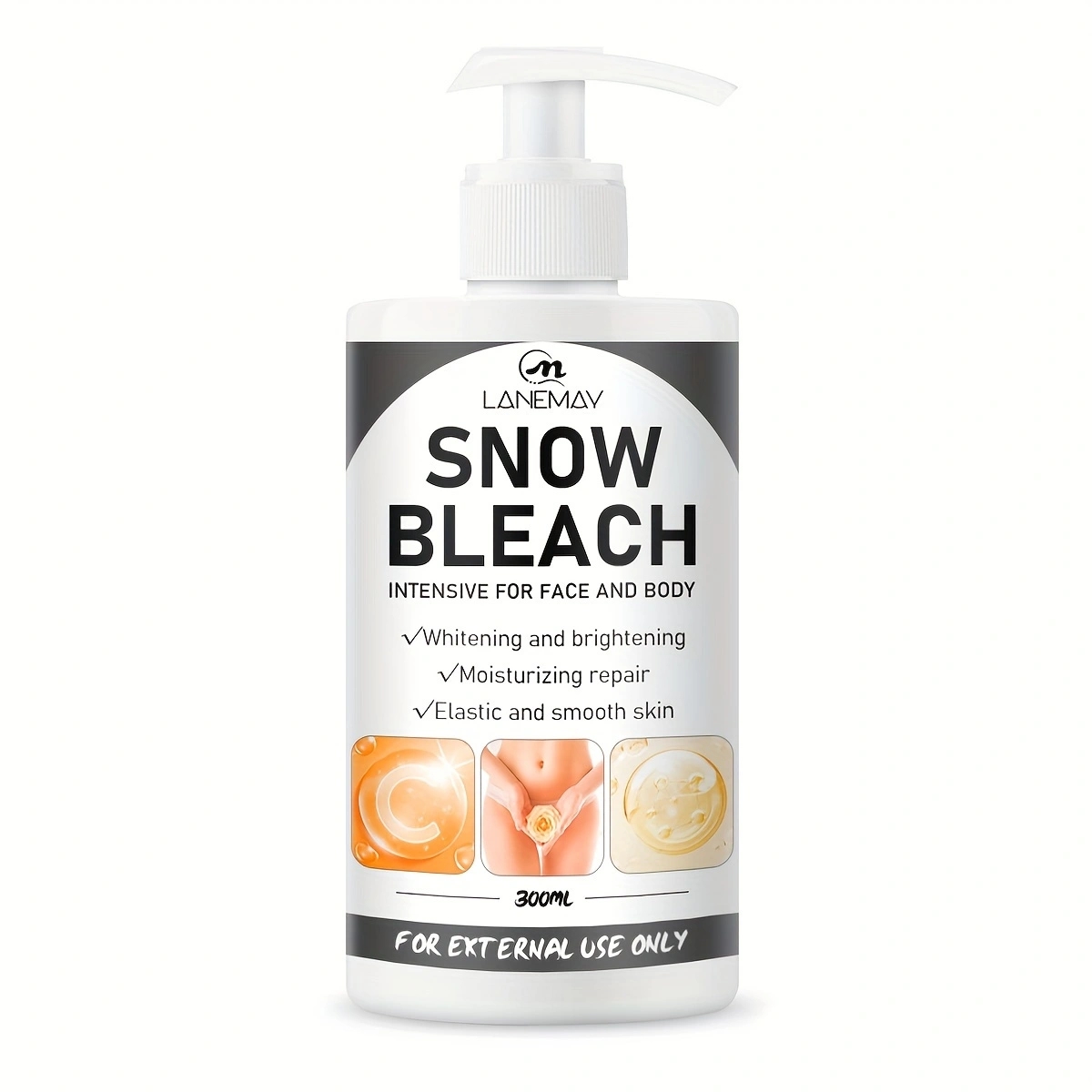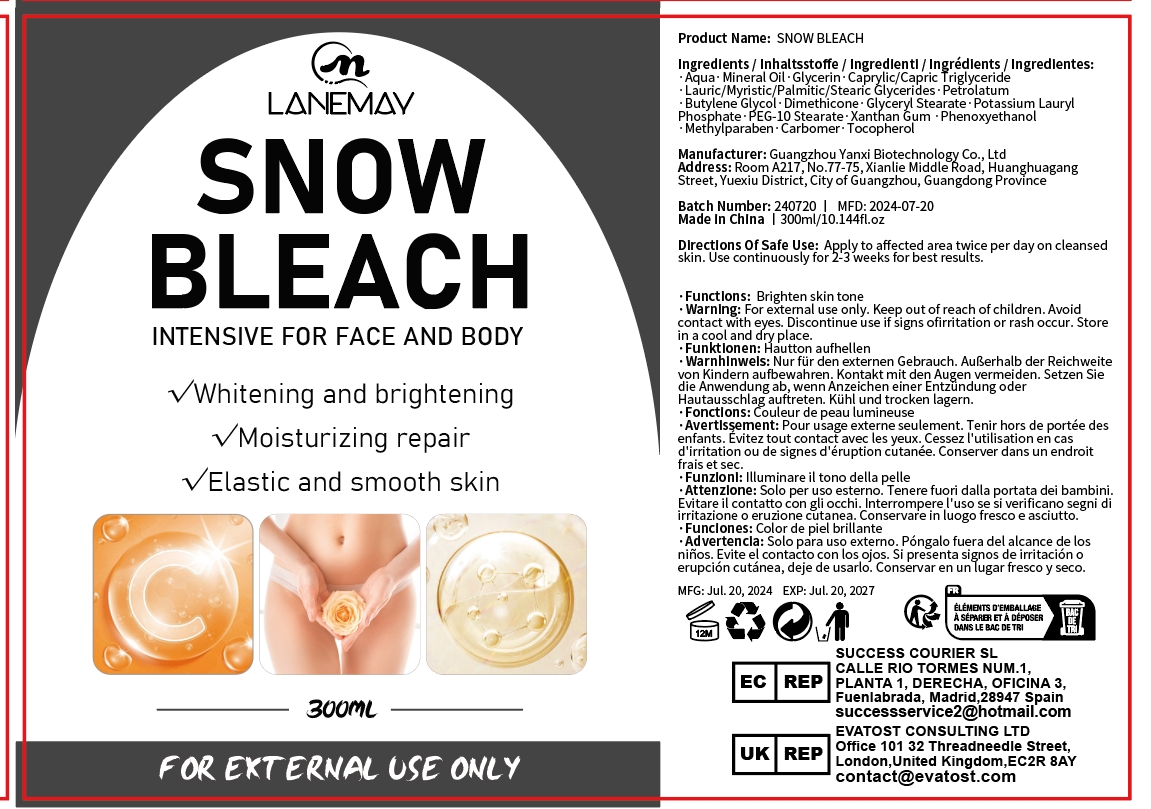 DRUG LABEL: SNOW BLEACH
NDC: 84025-126 | Form: CREAM
Manufacturer: Guangzhou Yanxi Biotechnology Co.. Ltd
Category: otc | Type: HUMAN OTC DRUG LABEL
Date: 20240808

ACTIVE INGREDIENTS: GLYCERIN 3 mg/300 mL; MINERAL OIL 5 mg/300 mL
INACTIVE INGREDIENTS: WATER

DOSAGE AND ADMINISTRATION

Cream for whitening and moisturizing body and face skin

WARNINGS

Keep out of children

INACTIVE INGREDIENT

Aqua

INDICATIONS AND USAGE

For daily skin care

Keep out of children

PURPOSE

Effectively repair and whiten skin